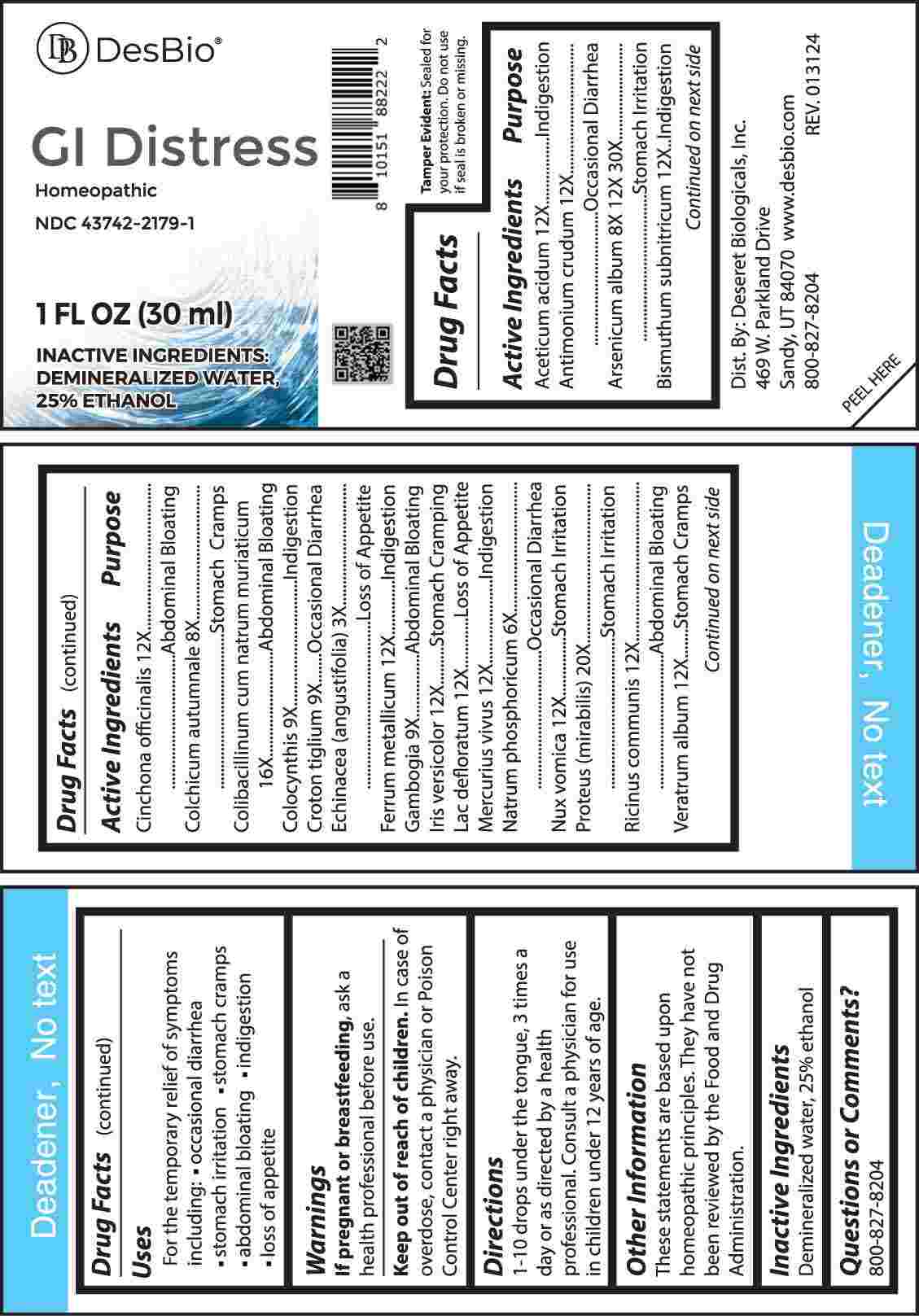 DRUG LABEL: GI Distress
NDC: 43742-2179 | Form: LIQUID
Manufacturer: Deseret Biologicals, Inc.
Category: homeopathic | Type: HUMAN OTC DRUG LABEL
Date: 20240513

ACTIVE INGREDIENTS: ACETIC ACID 12 [hp_X]/1 mL; ANTIMONY TRISULFIDE 12 [hp_X]/1 mL; ARSENIC TRIOXIDE 8 [hp_X]/1 mL; BISMUTH SUBNITRATE 12 [hp_X]/1 mL; CINCHONA OFFICINALIS BARK 12 [hp_X]/1 mL; COLCHICUM AUTUMNALE BULB 8 [hp_X]/1 mL; ESCHERICHIA COLI 16 [hp_X]/1 mL; CITRULLUS COLOCYNTHIS FRUIT PULP 9 [hp_X]/1 mL; CROTON TIGLIUM SEED 9 [hp_X]/1 mL; ECHINACEA ANGUSTIFOLIA WHOLE 3 [hp_X]/1 mL; IRON 12 [hp_X]/1 mL; GAMBOGE 9 [hp_X]/1 mL; IRIS VERSICOLOR ROOT 12 [hp_X]/1 mL; SKIM MILK 12 [hp_X]/1 mL; MERCURY 12 [hp_X]/1 mL; SODIUM PHOSPHATE, DIBASIC, HEPTAHYDRATE 6 [hp_X]/1 mL; STRYCHNOS NUX-VOMICA SEED 12 [hp_X]/1 mL; PROTEUS MIRABILIS 20 [hp_X]/1 mL; RICINUS COMMUNIS SEED 12 [hp_X]/1 mL; VERATRUM ALBUM ROOT 12 [hp_X]/1 mL
INACTIVE INGREDIENTS: WATER; ALCOHOL

DRUG FACTS:

ACTIVE INGREDIENT:

Aceticum Acidum 12X, Antimonium Crudum 12X, Arsenicum Album 8X, 12X, 30X, Bismuthum Subnitricum 12X, Cinchona Officinalis 12X, Colchicum Autumnale 8X, Colibacillinum Cum Natrum Muriaticum 16X, Colocynthis 9X, Croton Tiglium 9X, Echinacea (Angustifolia) 3X, Ferrum Metallicum 12X, Gambogia 9X, Iris Versicolor 12X, Lac Defloratum 12X, Mercurius Vivus 12X, Natrum Phosphoricum 6X, Nux Vomica 12X, Proteus (Mirabilis) 20X, Ricinus Communis 12X, Veratrum Album 12X.

PURPOSE:

Aceticum Acidum - Indigestion, Antimonium Crudum – Occasional Diarrhea, Arsenicum Album – Stomach Irritation, Bismuthum Subnitricum - Indigestion, Cinchona Officinalis – Abdominal Bloating, Colchicum Autumnale – Stomach Cramps, Colibacillinum Cum Natrum Muriaticum – Abdominal Bloating, Colocynthis - Indigestion, Croton Tiglium – Occasional Diarrhea, Echinacea (Angustifolia) – Loss of Appetite, Ferrum Metallicum - Indigestion, Gambogia – Abdominal Bloating, Iris Versicolor – Stomach Cramping, Lac Defloratum – Loss of Appetite, Mercurius Vivus - Indigestion, Natrum Phosphoricum – Occasional Diarrhea, Nux Vomica – Stomach Irritation, Proteus (Mirabilis) – Stomach Irritation, Ricinus Communis – Abdominal Bloating, Veratrum Album – Stomach Cramps

USES:

• For the temporary relief of symptoms including:

• occasional diarrhea • stomach cramps

• abdominal bloating • indigestion • loss of appetite

These statements are based upon homeopathic principles. They have not been reviewed by the Food and Drug Administration.

WARNINGS:

If pregnant or breast-feeding, ask a health professional before use.

Keep out of reach of children. In case of overdose, contact a physician or Poison Control Center right away.

Tamper Evident: Sealed for your protection. Do not use if seal is broken or missing.

KEEP OUT OF REACH OF CHILDREN:

In case of overdose, contact a physician or Poison Control Center right away.

DIRECTIONS:

1-10 drops under the tongue, 3 times a day or as directed by a health professional. Consult a physician for use in children under 12 years of age.

INACTIVE INGREDIENTS:

Demineralized water, 25% ethanol

QUESTIONS:

Dist. By: Deseret Biologicals, Inc.
469 W. Parkland Drive
Sandy, UT 84070

www.desbio.com

800-827-8204

PACKAGE LABEL DISPLAY:

DesBio

GI Distress

Homeopathic

NDC 43742-2179-1

1 FL OZ (30 ml)